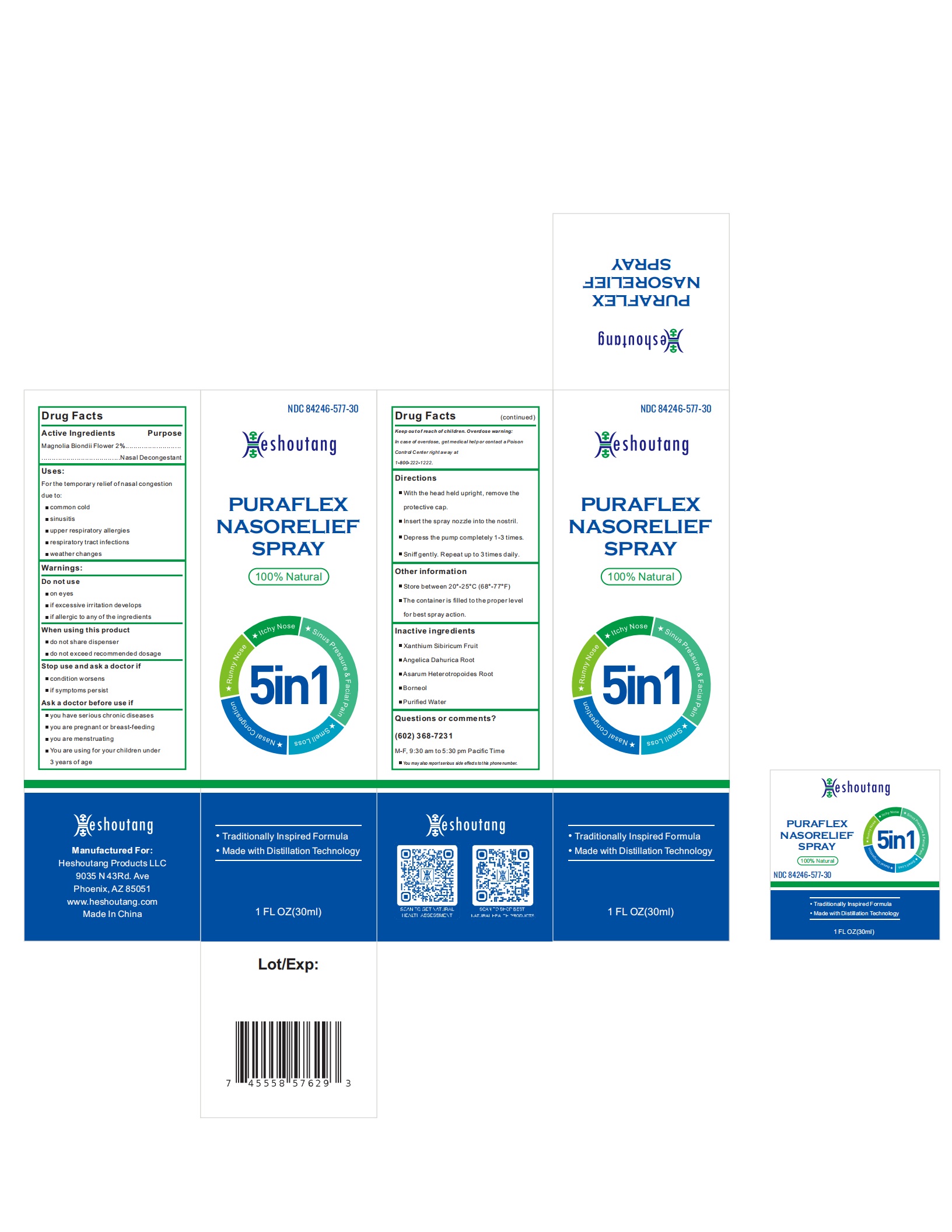 DRUG LABEL: Nasal Relief
NDC: 84246-577 | Form: LIQUID
Manufacturer: Shandong Huawei Pharmaceutical Co., Ltd.
Category: otc | Type: HUMAN OTC DRUG LABEL
Date: 20240515

ACTIVE INGREDIENTS: MAGNOLIA BIONDII FLOWER 2 g/100 mL
INACTIVE INGREDIENTS: XANTHIUM SIBIRICUM FRUIT; ANGELICA DAHURICA ROOT; ASARUM HETEROTROPOIDES ROOT; BORNEOL; WATER

Shandong Huawei Pharmaceutical Co., Ltd.

Active Ingredients

MAGNOLIA BIONDII FLOWER 2%

Purpose

Nasal Decongestant

Uses

For the temporary relief of nasal congestion due to:

- common cold
- sinusitis
- upper respiratory allergies
- respiratory tract infections
- weather changes

WARNINGS

Do not use

- on eyes
- if excessive irritation develops
- if allergic to any of the ingredients

When using this product

- do not share dispenser
- do not exceed recommended dosage

Stop use and ask a doctor if

- condition worsens
- if symptoms persist.

Ask a doctor before use if

- you have serious chronic diseases
- you are pregnant or breast-feeding
- you are menstruating
- you are using for your children under 3 years of age.

Keep out of reach of children. Overdose Warning:

In case of overdose, get medical help or contact a Poison Control Center right away at 1-800-222-1222.

Directions

- With the head held upright, remove the protective cap.
- Insert the spray nozzle into the nostril.
- Depress the pump completely 1-3 times.
- Sniff gently. Repeat up to 3 times daily.

Other information

• Store between 20°-25°C (68°-77°F)

• The container is filled to proper level for best spray action.

Inactive ingredients

MAGNOLIA BIONDII FLOWER, XANTHIUM SIBIRICUM FRUIT, ANGELICA DAHURICA ROOT, ASARUM HETEROTROPOIDES ROOT, BORNEOL, PURIFIED WATER

Questions or comments? (602) 368-7231

M-F, 9:30 am to 5:30 pm Pacific Time
You may also report serious side effects to this phone number.

Manufactured for Heshoutang Products LLC

9035 N 43rd Ave, Phoenix, AZ 85051, USA
www.heshoutang.com

Made in China